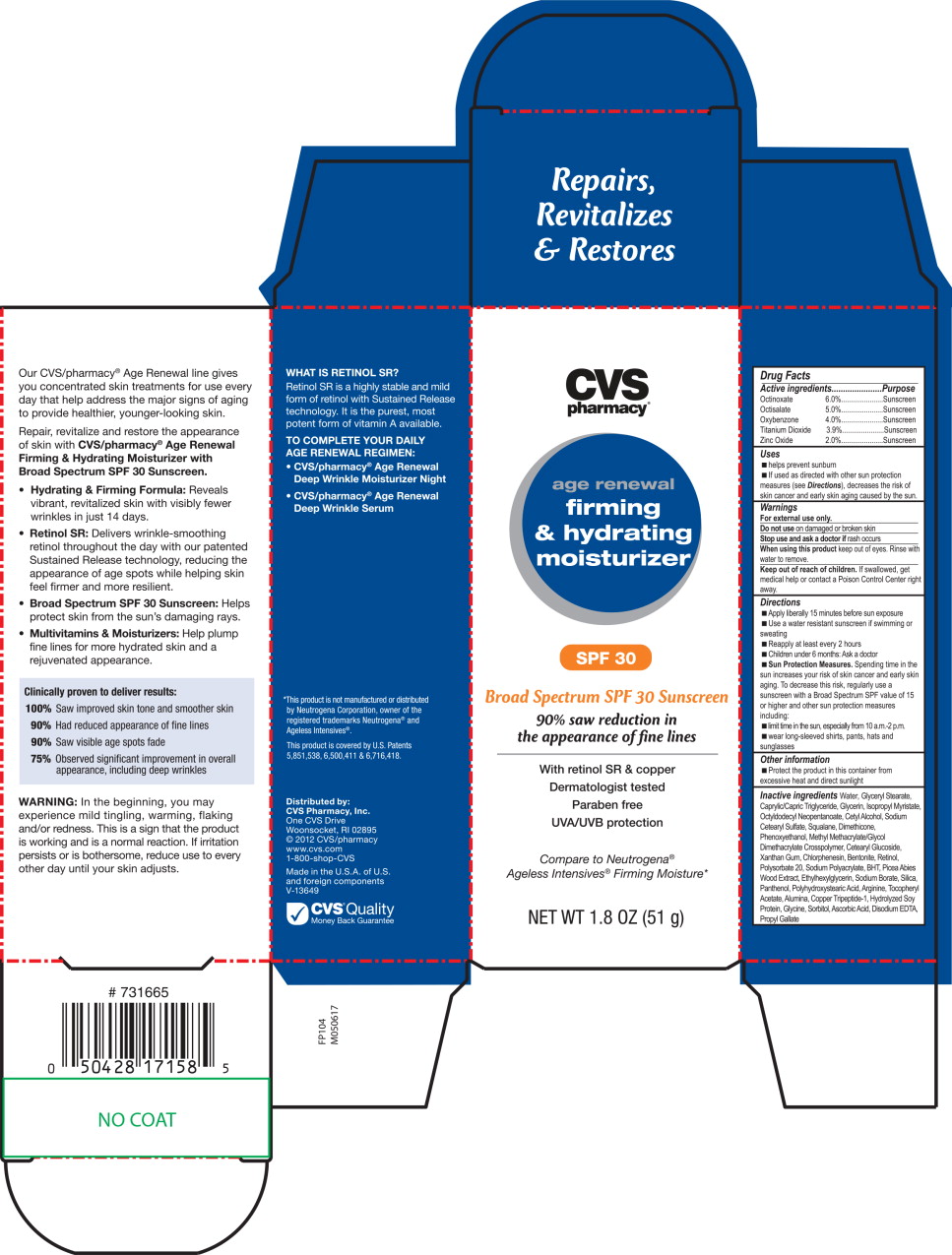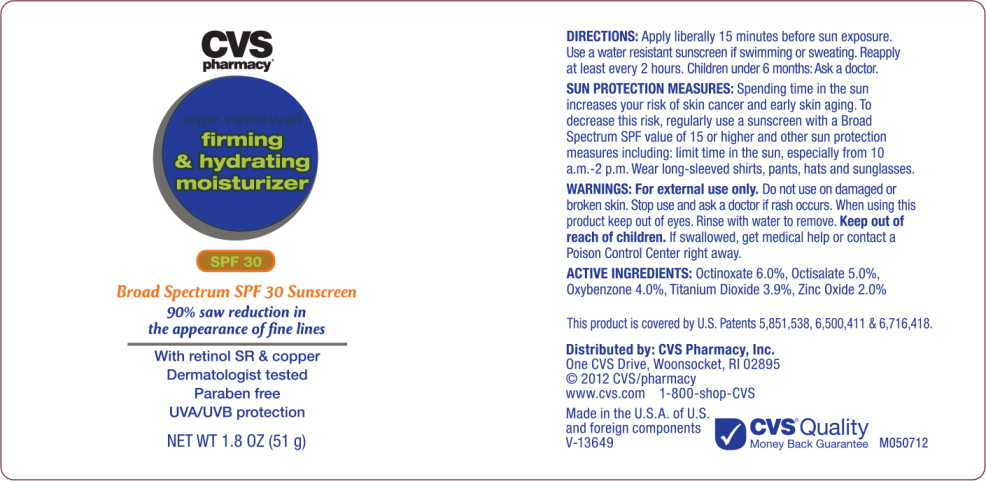 DRUG LABEL: Age Renewal Firming and Hydrating Moisturizer SPF 30
NDC: 69842-067 | Form: LOTION
Manufacturer: CVS Health
Category: otc | Type: HUMAN OTC DRUG LABEL
Date: 20170314

ACTIVE INGREDIENTS: octinoxate 60 mg/1 g; octisalate 50 mg/1 g; oxybenzone 40 mg/1 g; titanium dioxide 39 mg/1 g; zinc oxide 20 mg/1 g
INACTIVE INGREDIENTS: water; glyceryl monostearate; medium-chain triglycerides; glycerin; isopropyl myristate; cetyl alcohol; octyldodecyl neopentanoate; sodium cetostearyl sulfate; dimethicone; squalane; phenoxyethanol; methyl methacrylate/glycol dimethacrylate crosspolymer; cetearyl glucoside; xanthan gum; chlorphenesin; bentonite; retinol; polysorbate 20; sodium polyacrylate (8000 mw); butylated hydroxytoluene; ethylhexylglycerin; picea abies wood; sodium borate; silicon dioxide; panthenol; polyhydroxystearic acid (2300 mw); arginine; .alpha.-tocopherol acetate, DL-; aluminum oxide; prezatide copper; glycine; sorbitol; ascorbic acid; edetate disodium; propyl gallate

Drug Facts

Active ingredients

Octinoxate 6.0%

Octisalate 5.0%

Oxybenzone 4.0%

Titanium Dioxide 3.9%

Zinc Oxide 2.0%

Purpose

Sunscreen

Sunscreen

Sunscreen

Sunscreen

Sunscreen

Uses

- helps prevent sunburn
- If used as directed with other sun protection measures (see Directions), decreases the risk of skin cancer and early skin aging cause by the sun.

Warnings

For external use only.

Do not use on damaged or broken skin

Stop use and ask a doctor if rash occurs

When using this product keep out of eyes. Rinse with water to remove.

Keep out of reach of children. If swallowed, get medical help or contact a Poison Control Center right away.

Directions

- Apply liberally 15 minutes before sun exposure
- Use a water resistant sunscreen if swimming or sweating
- Reapply at least every 2 hours
- Children under 6 months: Ask a doctor
- Sun Protection Measures. Spending time in the sun increases your risk of skin cancer and early skin aging. To decrease this risk, regularly use a sunscreen with a Broad Spectrum SPF value of 15 or higher and other sun protection measures including:
  - limit time in the sun, especially from 10 a.m.-2 p.m.
  - wear long-sleeved shirts, pants, hats and sunglasses

Other information

- Protect the product in this container from excessive heat and direct sunlight

Inactive ingredients

Water, Glyceryl Stearate, Caprylic/Capric Triglyceride, Glycerin, Isopropyl Myristate, Octyldodecyl Neopentanoate, Cetyl Alcohol, Sodium Cetearyl Sulfate, Squalane, Dimethicone, Phenoxyethanol, Methyl Methacrylate/Glycol Dimethacrylate Crosspolymer, Cetearyl Glucoside, Xanthan Gum, Chlorphenesin, Bentonite, Retinol, Polysorbate 20, Sodium Polyacrylate, BHT, Picea Abies Wood Extract, Ethylhexylglycerin, Sodium Borate, Silica, Panthenol, Polyhydroxystearic Acid, Arginine, Tocopheryl Acetate, Alumina, Copper Tripeptide-1, Hydrolyzed Soy Protein, Glycine, Sorbitol, Ascorbic Acid, Disodium EDTA, Propyl Gallate

Principal Display Panel - Carton Label

CVS
pharmacy®

age renewal

firming
& hydrating
moisturizer

SPF 30

Broad Spectrum SPF 30 Sunscreen

90% saw reduction in
the appearance of fine lines

With retinol SR & copper

Dermatologist tested

Paraben free

UVA/UVB protection

Compare to Neutrogena®

Ageless Intensives® Firming Moisture*

NET WET 1.8 OZ (51 g)

Principal Display Panel - Bottle Label

CVS
pharmacy®

age renewal

firming
& hydrating
moisturizer

SPF 30

Broad Spectrum SPF 30 Sunscreen

90% saw reduction in
the appearance of fine lines

With retinol SR & copper

Dermatologist tested

Paraben free

UVA/UVB protection

NET WET 1.8 OZ (51 g)